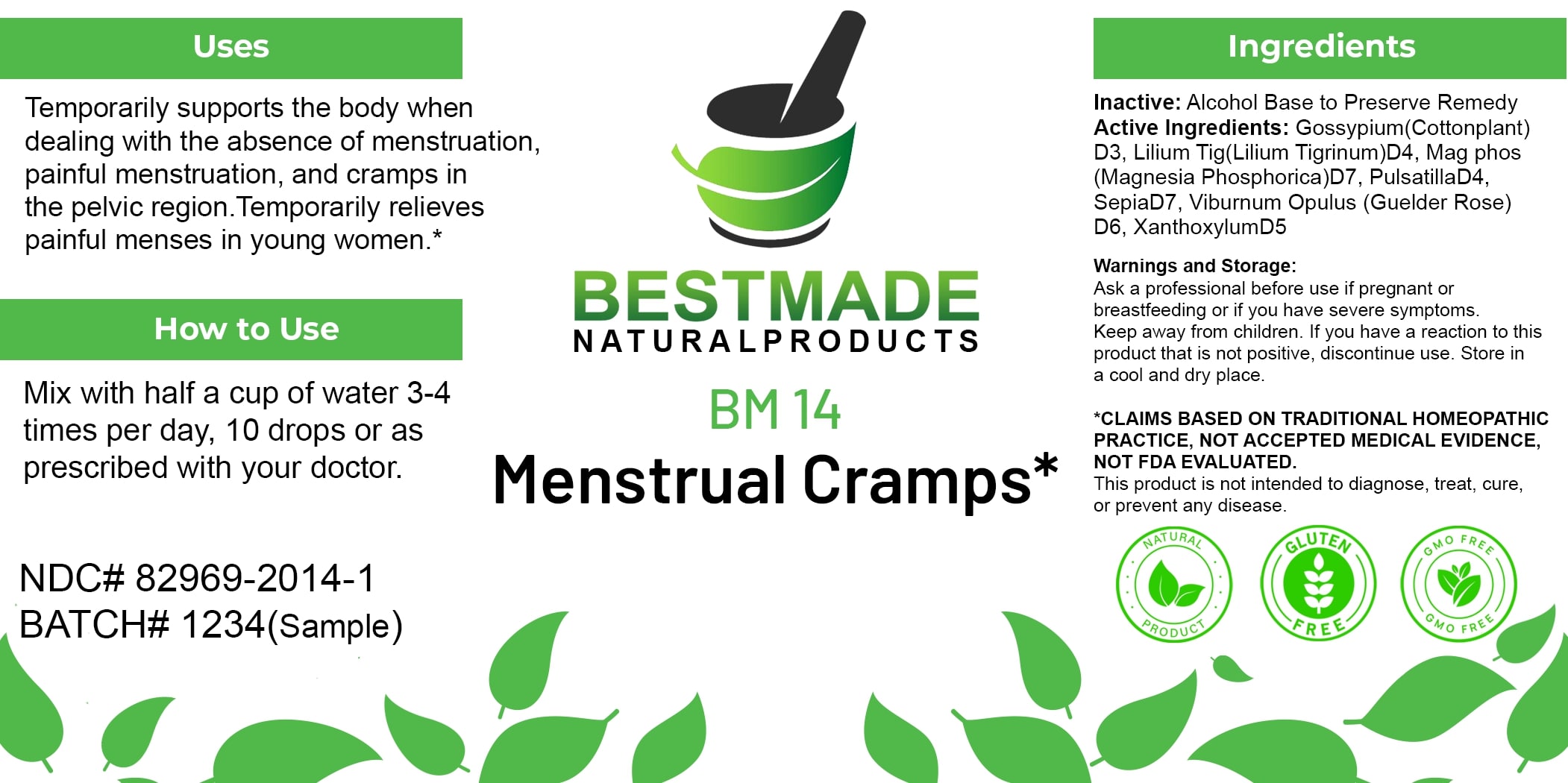 DRUG LABEL: Bestmade Natural Products BM14
NDC: 82969-2014 | Form: LIQUID
Manufacturer: Bestmade Natural Products
Category: homeopathic | Type: HUMAN OTC DRUG LABEL
Date: 20250122

ACTIVE INGREDIENTS: GOSSYPIUM HERBACEUM ROOT BARK 30 [hp_C]/30 [hp_C]; MAGNESIUM PHOSPHATE, DIBASIC TRIHYDRATE 30 [hp_C]/30 [hp_C]; ZANTHOXYLUM AMERICANUM BARK 30 [hp_C]/30 [hp_C]; SEPIA OFFICINALIS JUICE 30 [hp_C]/30 [hp_C]; LILIUM LANCIFOLIUM WHOLE FLOWERING 30 [hp_C]/30 [hp_C]; PULSATILLA PRATENSIS 30 [hp_C]/30 [hp_C]; VIBURNUM OPULUS BARK 30 [hp_C]/30 [hp_C]
INACTIVE INGREDIENTS: ALCOHOL 30 [hp_C]/30 [hp_C]

BM14

DOSAGE AND ADMINISTRATION

How to Use
Mix with half a cup of water 3-4 times per day, 10 drops or as prescribed with your doctor.

INACTIVE INGREDIENT

Ingredients
Inactive: Alcohol Base to Preserve Remedy

Uses
Temporarily supports the body when dealing with the absence of menstruation, painful menstruation, and cramps in the pelvic region. Temporarily relieves painful menses in young women.*

*CLAIMS BASED ON TRADITIONAL HOMEOPATHIC PRACTICE, NOT ACCEPTED MEDICAL EVIDENCE, NOT FDA EVALUATED.
This product is not intended to diagnose, treat, cure, or prevent any disease.

ACTIVE INGREDIENT

Active Ingredients: Gossypium (Cottonplant) D3, Lilium Tig (Lilium Tigrinum) D4, Mag phos (Magnesia Phosphorica) D7, Pulsatilla D4, Sepia D7, Viburnum Opulus (Guelder Rose) D6, Xanthoxylum D5

KEEP OUT OF REACH OF CHILDREN

Warnings and Storage:
Ask a professional before use if pregnant or breastfeeding or if you have severe symptoms.
Keep away from children. If you have a reaction to this product that is not positive, discontinue use. Store in a cool and dry place.

Uses
Temporarily supports the body when dealing with the absence of menstruation, painful menstruation, and cramps in the pelvic region. Temporarily relieves painful menses in young women.*

*CLAIMS BASED ON TRADITIONAL HOMEOPATHIC PRACTICE, NOT ACCEPTED MEDICAL EVIDENCE, NOT FDA EVALUATED.
This product is not intended to diagnose, treat, cure, or prevent any disease.

Warnings and Storage:
Ask a professional before use if pregnant or breastfeeding or if you have severe symptoms.
Keep away from children. If you have a reaction to this product that is not positive, discontinue use. Store in a cool and dry place.

*CLAIMS BASED ON TRADITIONAL HOMEOPATHIC PRACTICE, NOT ACCEPTED MEDICAL EVIDENCE, NOT FDA EVALUATED.
This product is not intended to diagnose, treat, cure, or prevent any disease.

Entire package label